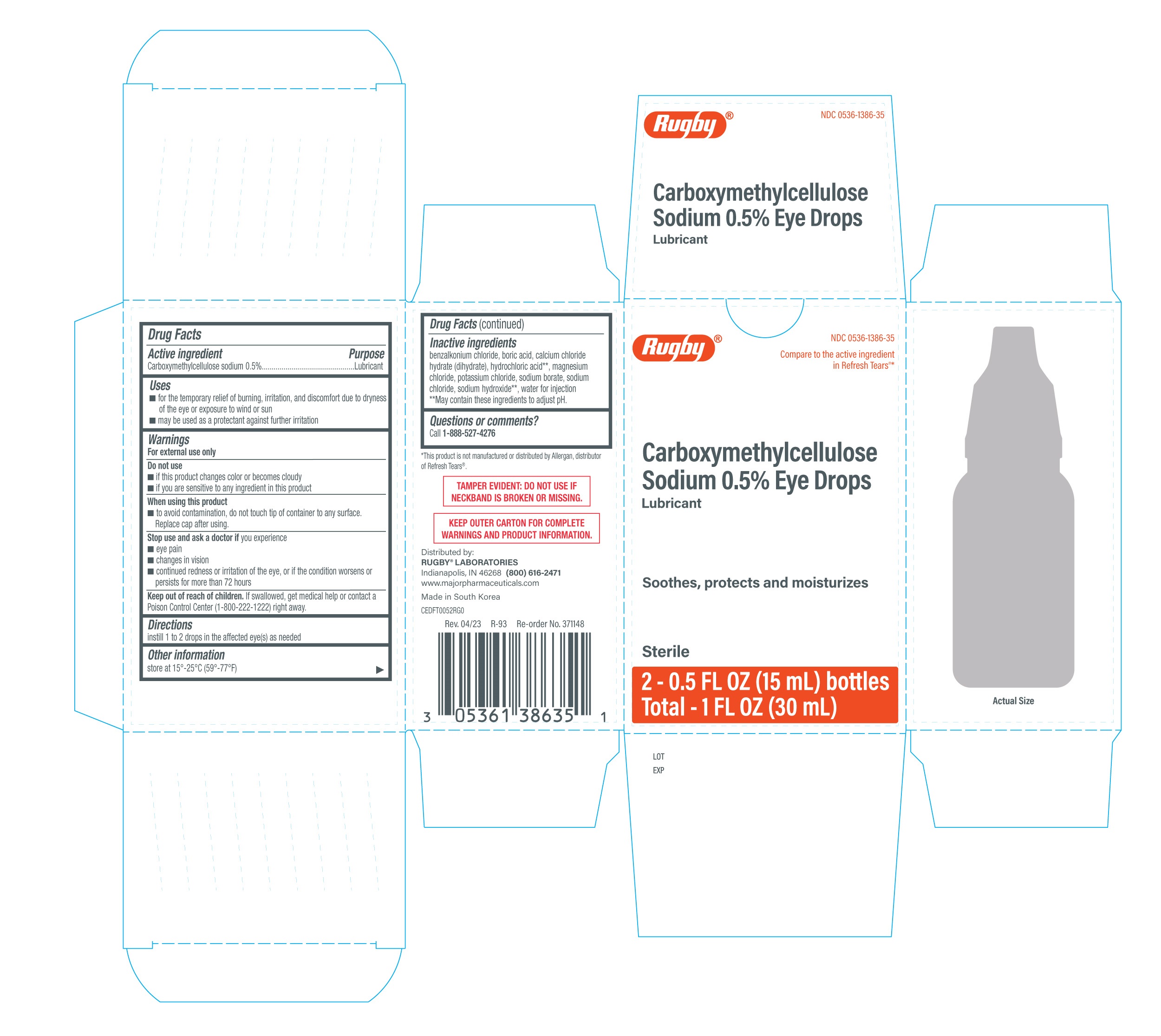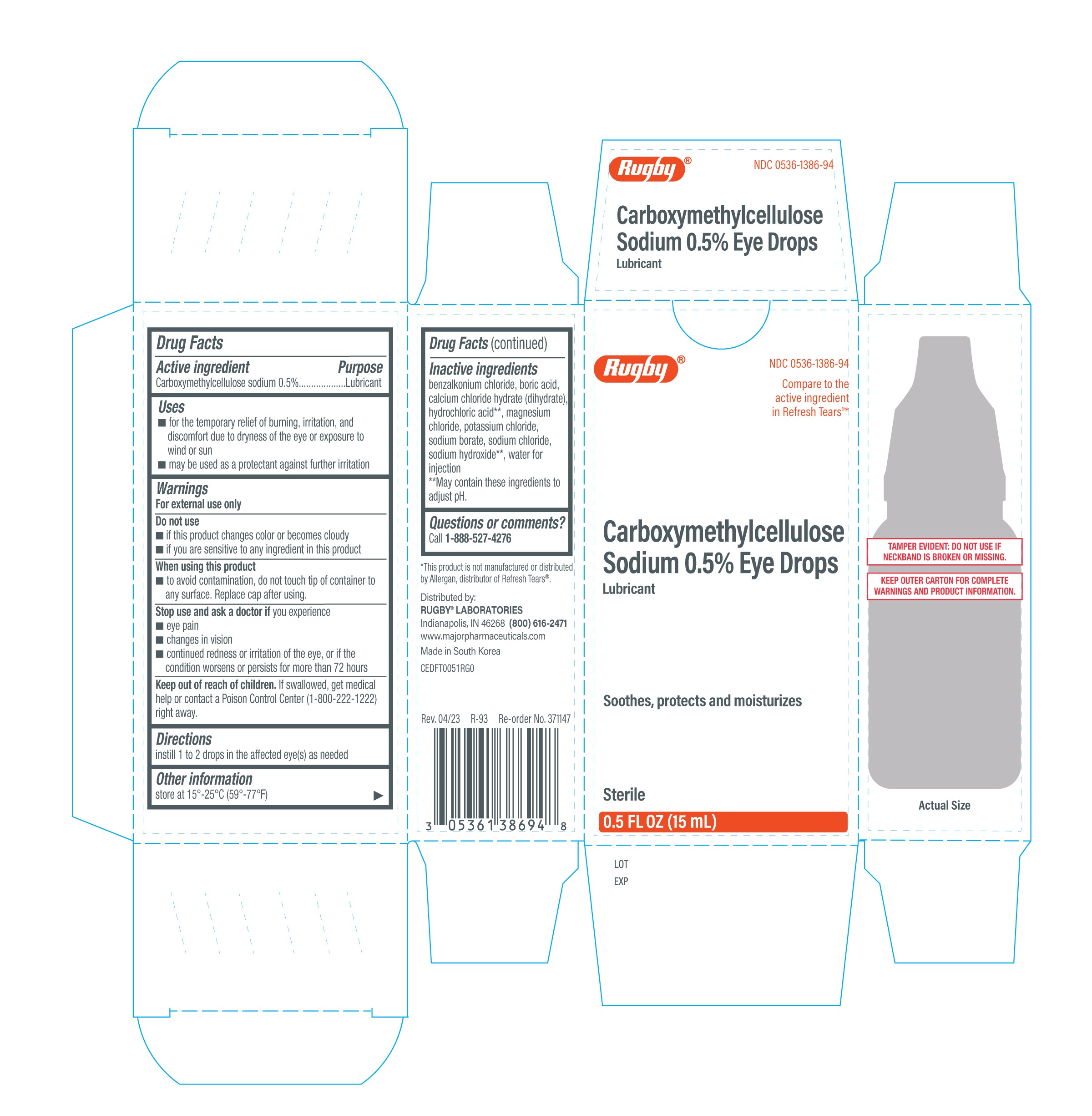 DRUG LABEL: Rugby Carboxymethylcellulose Sodium 0.5% Eye Drops
NDC: 0536-1386 | Form: SOLUTION/ DROPS
Manufacturer: Rugby Laboratories
Category: otc | Type: HUMAN OTC DRUG LABEL
Date: 20251230

ACTIVE INGREDIENTS: CARBOXYMETHYLCELLULOSE SODIUM 0.5 g/100 mL
INACTIVE INGREDIENTS: BORIC ACID; POTASSIUM CHLORIDE; WATER; CALCIUM CHLORIDE; HYDROCHLORIC ACID; MAGNESIUM CHLORIDE; SODIUM HYDROXIDE; SODIUM CHLORIDE; SODIUM BORATE; BENZALKONIUM CHLORIDE

Rugby Carboxymethylcellulose Sodium 0.5% Eye Drops (PLD)

Active ingredient

Carboxymethylcellulose sodium 0.5%

Purpose

Lubricant

Uses

- for the temporary relief of burning, irritation, and, discomfort due to dryness of the eye or exposure to wind or sun
- may be used as a protectant against further irritation

Warnings

For external use only

Do not use

- if this product changes color or becomes cloudy
- if you are sensitive to any ingredient in this product

When using this product

- to avoid contamination, do not touch tip of container to any surface. Replace cap after using.

Stop use and ask a doctor if you experience

- eye pain
- changes in vision
- continued redness or irritation of the eye, or if the condition worsens or persists for more than 72 hours

Keep out of reach of children.

If swallowed, get medical help or contact a Poison Control Center (1-800-222-1222) right away.

Directions

instill 1 to 2 drops in the affected eye(s) as needed

Other information

store at 15°-25°C (59°-77°F)

Inactive ingredients

benzalkonium chloride, boric acid, calcium chloride hydrate (dihydrate), hydrochloric acid**, magnesium chloride, potassium chloride, sodium borate, sodium chloride, sodium hydroxide**, water for injection

**May contain these ingredients to adjust pH.

Questions or comments?

Call 1-888-527-4276